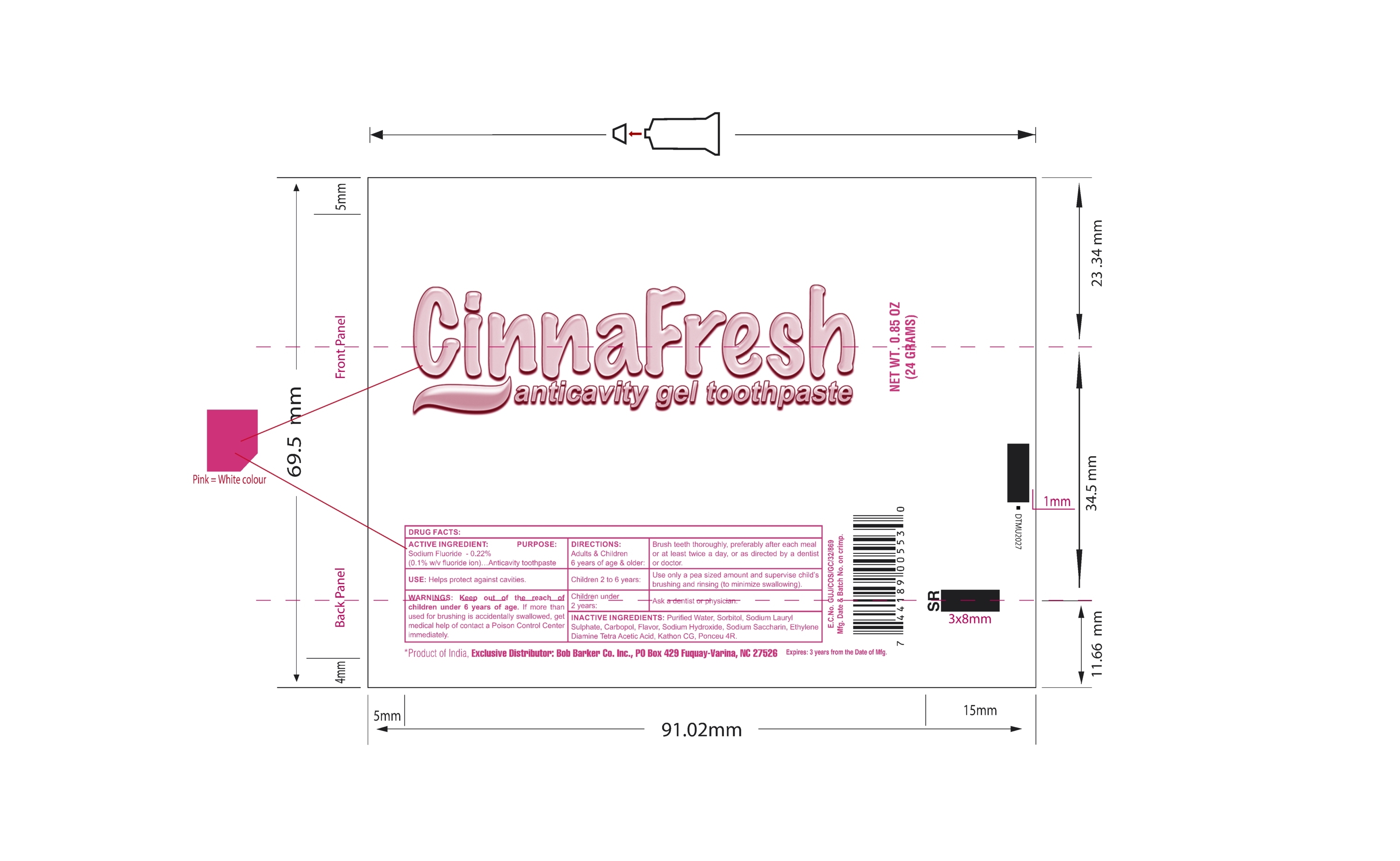 DRUG LABEL: Cinnafresh AntiCavity
NDC: 76001-003 | Form: GEL, DENTIFRICE
Manufacturer: Daxal Cosmetics Private Limited
Category: otc | Type: HUMAN OTC DRUG LABEL
Date: 20190815

ACTIVE INGREDIENTS: SODIUM FLUORIDE 0.22 g/100 g
INACTIVE INGREDIENTS: PONCEAU 4R; SODIUM HYDROXIDE; WATER; SORBITOL; SILICON DIOXIDE; SODIUM LAURYL SULFATE; CARBOMER HOMOPOLYMER, UNSPECIFIED TYPE; SACCHARIN SODIUM; EDETATE DISODIUM; METHYLCHLOROISOTHIAZOLINONE/METHYLISOTHIAZOLINONE MIXTURE

Cinnafresh AntiCavity Gel Toothpaste

ACTIVE INGREDIENT

Sodium Fluoride - 0.22% (0.1% w/v fluoride ion)

DRUG FACTS

PURPOSE

Anticavity Toothpaste.

USE

Helps protect against cavities.

WARNINGS

Keep out of reach of children under 6 years of age. If more than used for brushing is accidentally swallowed, get medical help or contact a Poison Control Center immediately.

DIRECTIONS:

Adults & Children 6 years of age & older : Brush teeth throughly, preferably after each meal or at least twice a day, or as directed by a dentist or doctor.

Children 2 to 6 years : Use only a pea sized amount and supervise child's brushing and rinsing (to minimize swallowing).

Children under 2 years : Ask a dentist or physician.

INACTIVE INGREDIENTS:

Purified Water, Sorbitol, Sodium Lauryl Sulphate, Carbopol, Flavor, Sodium Hydroxide, Sodium Saccharin, Ethylene Diamine Tetra Acetic Acid, Kathon CG, Ponceu 4R.